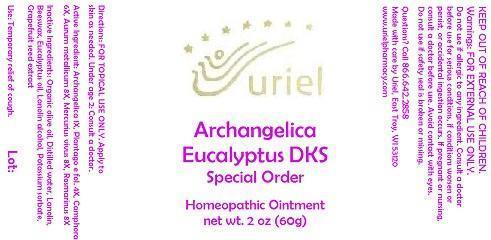 DRUG LABEL: Archangelica Eucalyptus DKS Special Order
NDC: 48951-1268 | Form: OINTMENT
Manufacturer: Uriel Pharmacy Inc.
Category: homeopathic | Type: HUMAN OTC DRUG LABEL
Date: 20150220

ACTIVE INGREDIENTS: ANGELICA ARCHANGELICA ROOT 1 [hp_X]/1 g; PLANTAGO MAJOR LEAF 4 [hp_X]/1 g; CAMPHOR (NATURAL) 6 [hp_X]/1 g; GOLD 8 [hp_X]/1 g; MERCURY 8 [hp_X]/1 g; ROSMARINUS OFFICINALIS FLOWERING TOP 8 [hp_X]/1 g
INACTIVE INGREDIENTS: OLIVE OIL; WATER; LANOLIN; YELLOW WAX; EUCALYPTUS OIL; LANOLIN ALCOHOLS; POTASSIUM SORBATE; CITRUS PARADISI SEED

Archangelica Eucalyptus DKS Special Order

INDICATIONS AND USAGE

Directions: FOR TOPICAL USE ONLY.

DOSAGE AND ADMINISTRATION

Apply to skin as needed. Under age 2: Consult a doctor.

Active Ingredient: Archangelica 1X, Plantago e fol. 4X, Camphora 6X, Aurum metallicum 8X, Mercurius vivus 8X, Rosmarinus 8X

INACTIVE INGREDIENT

Inactive Ingredients: Organic olive oil, Distilled water, Lanolin, Beeswax, Eucalyptus oil, Lanolin alcohol, Potassium sorbate, Grapefruit seed extract

PURPOSE

Use: Temporary relief of cough.

KEEP OUT OF REACH OF CHILDREN.

WARNINGS

Warnings: FOR EXTERNAL USE ONLY. Do not use if allergic to any ingredient. Consult a doctor before use for serious conditions, if conditions worsen or persist, or accidental ingestion occurs. If pregnant or nursing, consult a doctor before use. Avoid contact with eyes. Do not use if safety seal is broken or missing.

QUESTIONS

Questions? Call 866.642.2858 Made with care by Uriel, East Troy, WI 53120 www.urielpharmacy.com